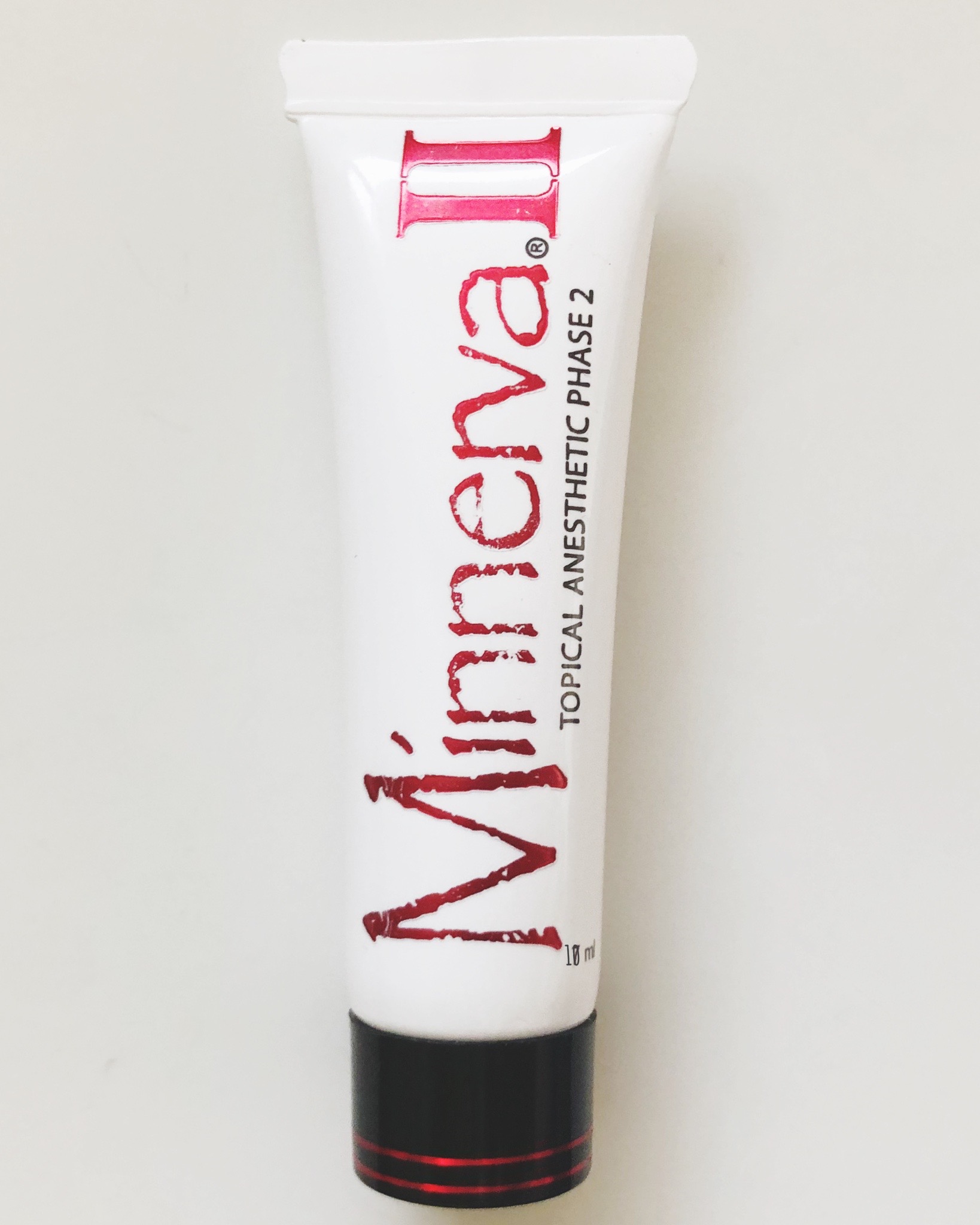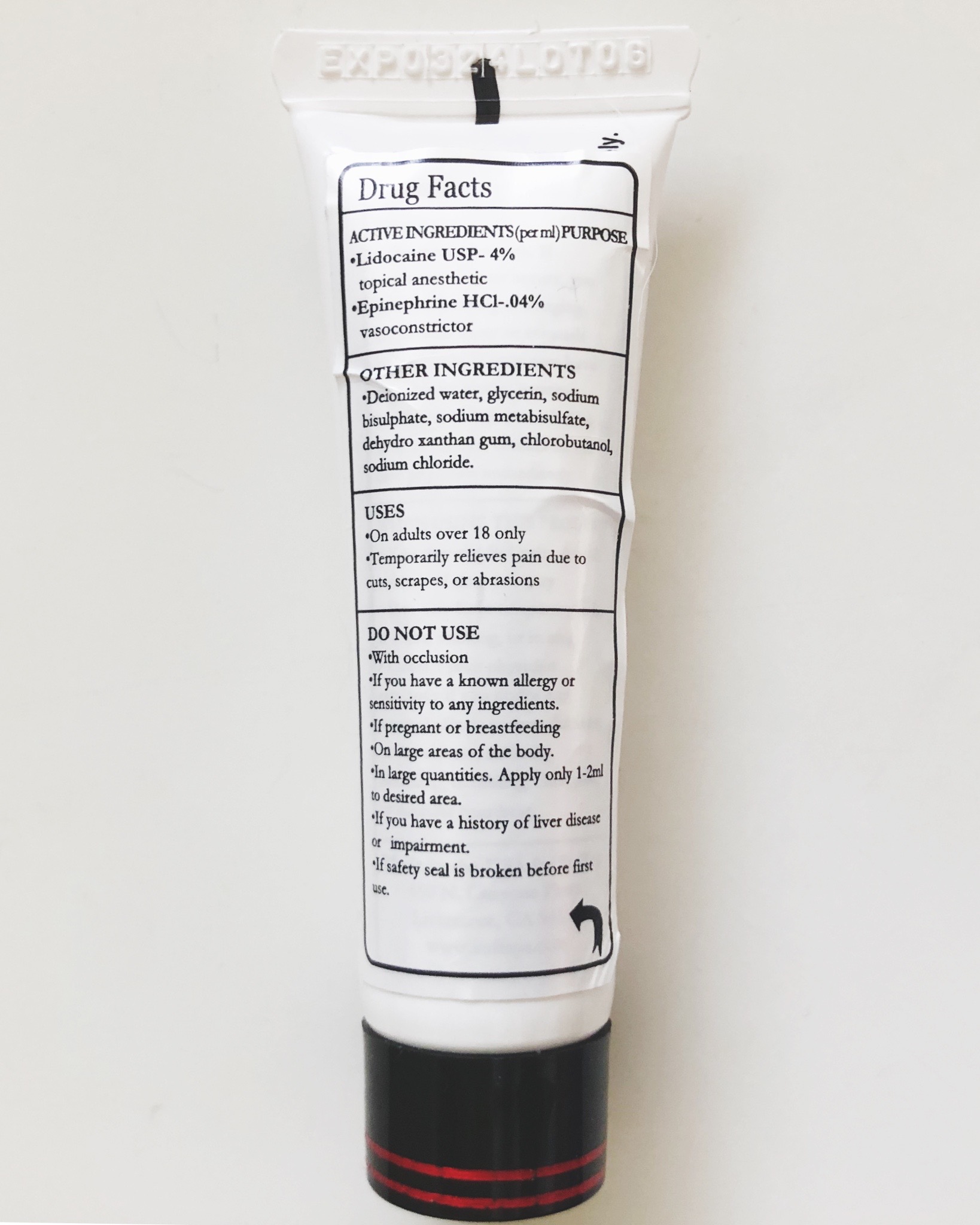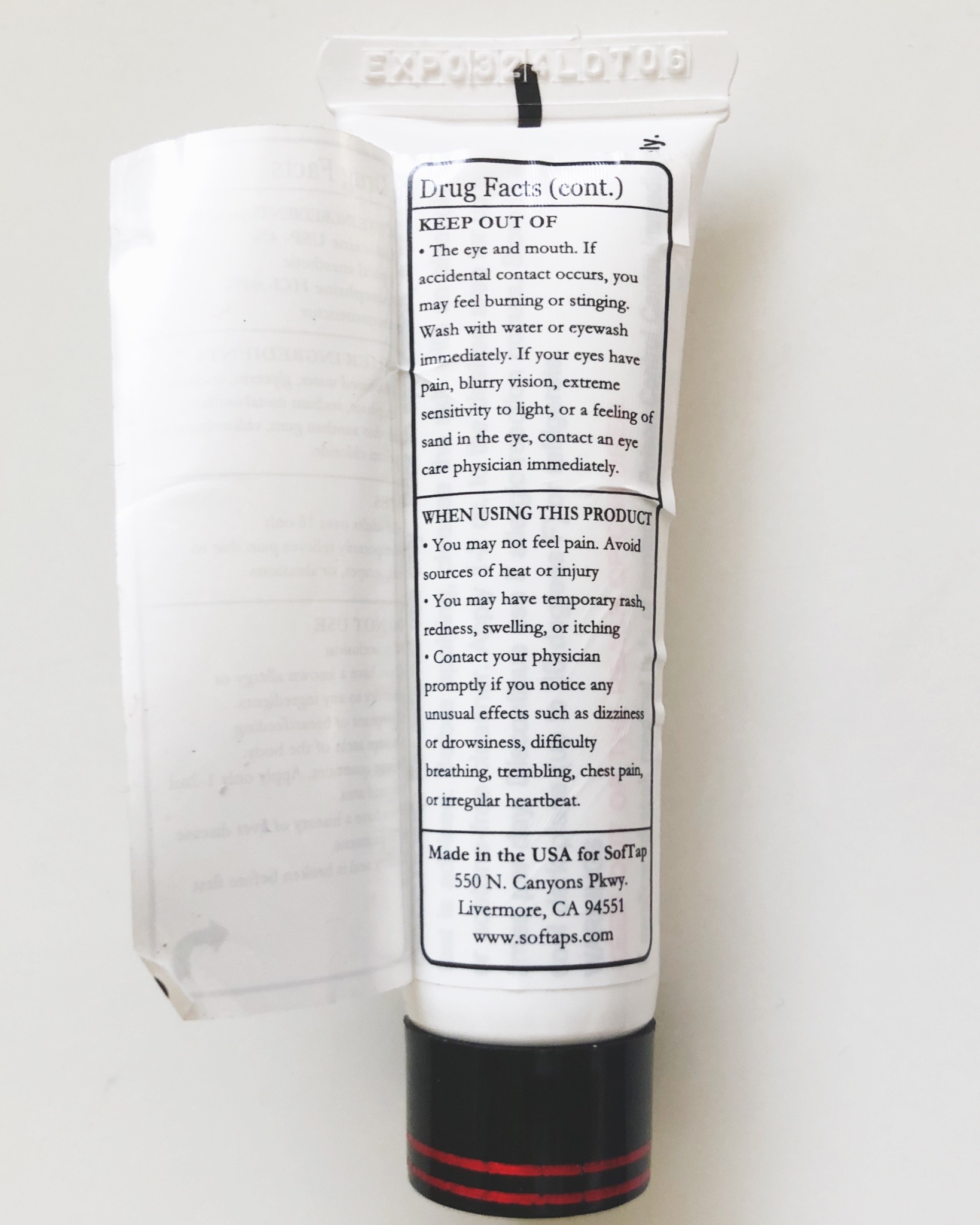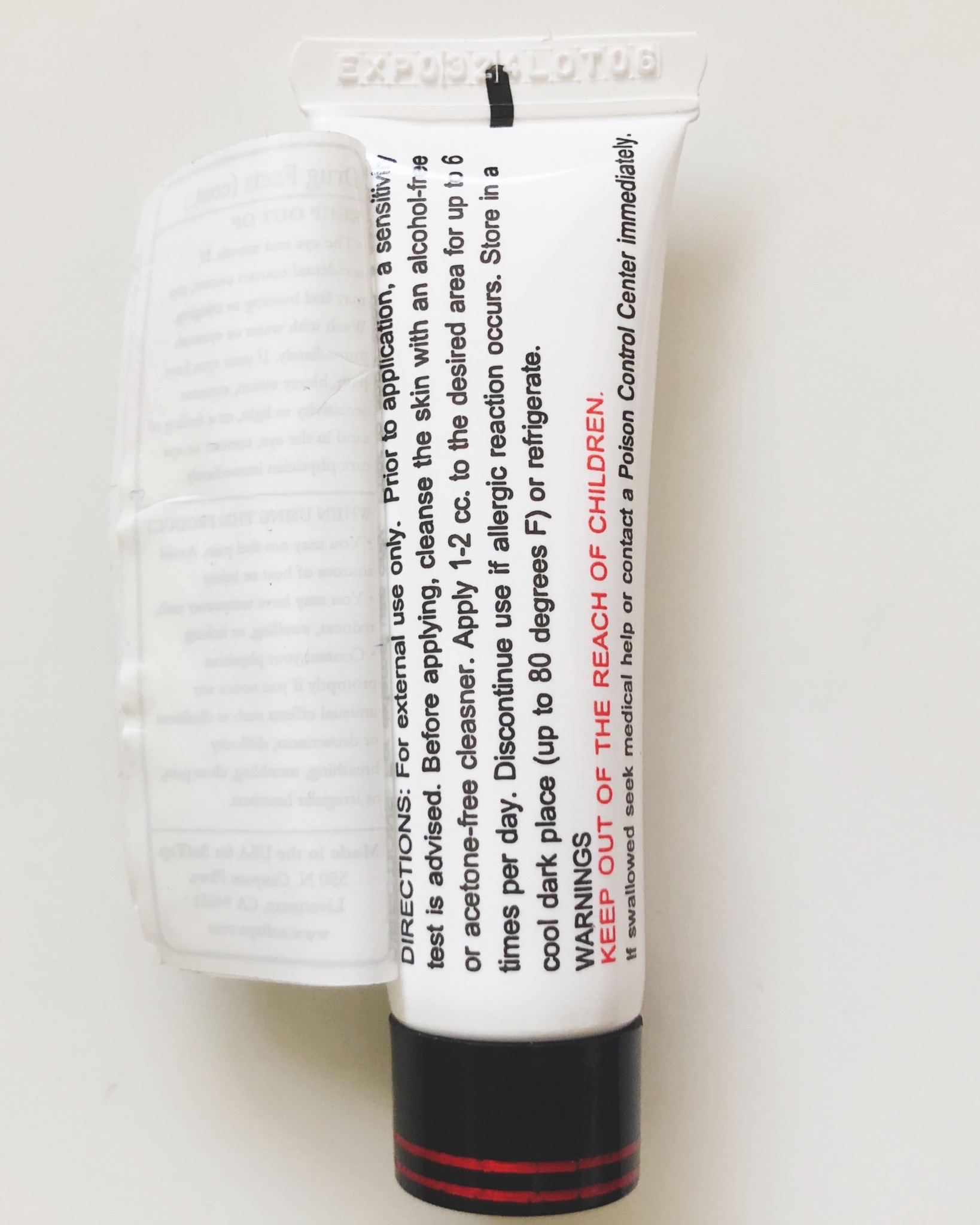 DRUG LABEL: Minnerva II
NDC: 82718-2210 | Form: GEL
Manufacturer: SofTap Inc
Category: otc | Type: HUMAN OTC DRUG LABEL
Date: 20220505

ACTIVE INGREDIENTS: EPINEPHRINE HYDROCHLORIDE 0.004 g/10 g; LIDOCAINE 0.3 g/10 g
INACTIVE INGREDIENTS: SODIUM METABISULFITE; CHLOROBUTANOL; SODIUM CHLORIDE; GLYCERIN; WATER; SODIUM BISULFATE; DEHYDROXANTHAN GUM

DRUG FACTS

ACTIVE INGREDIENTS (per ml) PURPOSE

- Lidocaine USP - 4%

topical anesthetic

- Epinephrine HCl - 0.4%

vasoconstrictor

OTHER INGREDIENTS

- Deionized water, glycerin, sodium bisulphate, sodium metabisulfate, dehydroxanthan gum, chlorobutanol, sodium chloride

DO NOT USE

- With occlusion
- If you have a known allergy or sensitivity to any ingredients.
- If pregnant or breastfeeding
- On large areas of the body
- In large quantities. Apply only 1-2ml to desired area
- If you have a history of liver disease or impairment
- If safety seal is broken before first use

KEEP OUT OF

- The eye and mouth. If accidental contact occurs, you may feel burning or stinging. Wash with water or eyewash immediately. If your eyes have pain, blurry vision, extreme sensitivity to light, or a feeling of sand in the eye, contact an eye care physician immediately.

WHEN USING THIS PRODUCT

- You may not feel pain. Avoid sources of heat or injury.
- You may have temporary rash, redness, swelling, or itching
- Contact your physician promptly if you notice any unusual effects such as dizziness or drowsiness, difficulty breathing, trembling, chest pain, or irregular heartbeat.

Made in the USA for SofTap

550 N Canyons Pkwy

Livermore, CA 94551

www.softaps.com

DIRECTIONS

For external use only. Prior to application, a sensitivity test is advised. Before applying, cleanse the skin with an alcohol-free or acetone-free cleanser. Apply 1-2 cc to the desired area for up to 6 times per day. Discontinue use if allergic reaction occurs. Store in a cool dark place (up to 80 degrees F) or refrigerate.

WARNINGS

KEEP OUT OF REACH OF CHILDREN

If swallowed seek medical help or contact Poison Control Center immediately.

USES

- On adults over 18 only
- Temporarily relieves pain due to cuts, scrapes, or abrasions

WARNINGS

KEEP OUT OF REACH OF CHILDREN

ACTIVE INGREDIENTS (per ml) PURPOSE

- Lidocaine USP - 4%

topical anesthetic

- Epinephrine HCl - .04%

vasoconstrictor